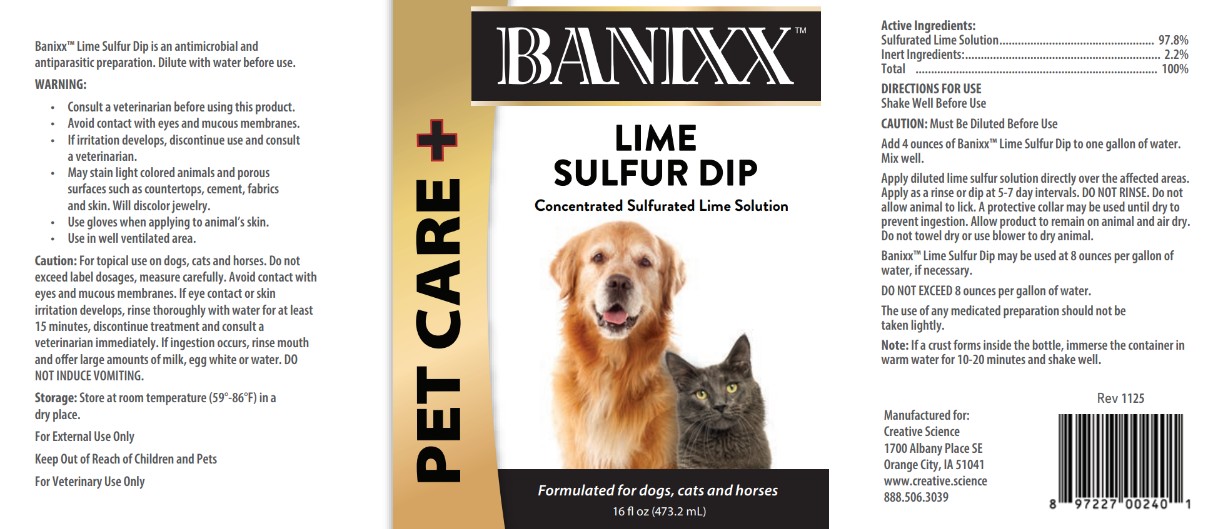 DRUG LABEL: Banixx Lime Sulfur Dip
NDC: 86099-209 | Form: SOLUTION, CONCENTRATE
Manufacturer: Creative Science
Category: animal | Type: OTC ANIMAL DRUG LABEL
Date: 20251205

ACTIVE INGREDIENTS: CALCIUM POLYSULFIDE 290 mg/1 g

INDICATIONS AND USAGE

Banixx™ Lime Sulfur Dip is an antimicrobial and
antiparasitic preparation. Dilute with water before use.

WARNING:
Consult a veterinarian before using this product.
Avoid contact with eyes and mucous membranes.
If irritation develops, discontinue use and consult
a veterinarian.
May stain light colored animals and porous
surfaces such as countertops, cement, fabrics
and skin. Will discolor jewelry.
Use gloves when applying to animal’s skin.
Use in well ventilated area.
Caution: For topical use on dogs, cats and horses. Do not
exceed label dosages, measure carefully. Avoid contact with
eyes and mucous membranes. If eye contact or skin
irritation develops, rinse thoroughly with water for at least
15 minutes, discontinue treatment and consult a
veterinarian immediately. If ingestion occurs, rinse mouth
and offer large amounts of milk, egg white or water. DO
NOT INDUCE VOMITING.

STORAGE AND HANDLING

Storage: Store at room temperature (59°-86°F) in a
dry place.

KEEP OUT OF REACH OF CHILDREN

For External Use Only
Keep Out of Reach of Children and Pets
For Veterinary Use Only

Active Ingredients:
Sulfurated Lime Solution.................................................. 97.8%

INACTIVE INGREDIENT

Inert Ingredients:............................................................... 2.2%
Total .............................................................................. 100%

DIRECTIONS FOR USE
Shake Well Before Use
CAUTION: Must Be Diluted Before Use
Add 4 ounces of Banixx™ Lime Sulfur Dip to one gallon of water.
Mix well.
Apply diluted lime sulfur solution directly over the affected areas.
Apply as a rinse or dip at 5-7 day intervals. DO NOT RINSE. Do not
allow animal to lick. A protective collar may be used until dry to
prevent ingestion. Allow product to remain on animal and air dry.
Do not towel dry or use blower to dry animal.
Banixx™ Lime Sulfur Dip may be used at 8 ounces per gallon of
water, if necessary.

WARNINGS AND PRECAUTIONS

DO NOT EXCEED 8 ounces per gallon of water.
The use of any medicated preparation should not be
taken lightly.
Note: If a crust forms inside the bottle, immerse the container in
warm water for 10-20 minutes and shake well.

Manufactured for:
Creative Science
1700 Albany Place SE
Orange City, IA 51041
www.creative.science
888.506.3039

Rev 1125

UPC 897227002401

PACKAGE LABEL

PET CARE

BANIXX LIME SULFUR DIP

Concentrated Sulfurated Lime Solution

Formulated for dogs, cats and horses

16 fl oz (473.2 mL)